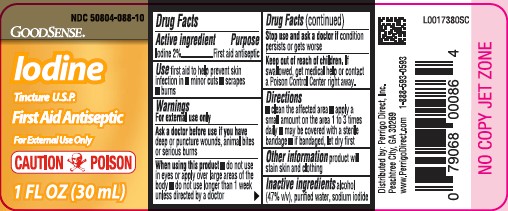 DRUG LABEL: Iodine
NDC: 50804-088 | Form: LIQUID
Manufacturer: Perrigo Direct, Inc
Category: otc | Type: HUMAN OTC DRUG LABEL
Date: 20260219

ACTIVE INGREDIENTS: IODINE 20 mg/1 mL; SODIUM IODIDE 20.4 mg/1 mL; ALCOHOL 470 mg/1 mL
INACTIVE INGREDIENTS: WATER

Good Sense 088.000/088AA
Iodine Tincture USP

Active Ingredient

Iodine 2%

Purpose

First aid antiseptic

Use

First aid to help prevent skin infection in

- minor cuts
- scrapes
- burns

Warnings

For external use only

Ask a doctor before use if you have

deep or puncture wounds, animal bites or serious burns.

When using this product

- do not use in eyes or apply over large areas of the body
- do not use longer than 1 week unless directed by a doctor

Stop use and ask a doctor if

condition persists or gets worse

Keep out of reach of children.

If swallowed, get medical help or contact a Poison Control Center right away.

Directions

- clean the affected area
- apply a small amount on the area 1 to 3 times daily
- may be covered with a sterile bandage
- if bandaged, let dry first

Other information

product will stain skin and clothing

Inactive ingredients

alcohol (47% v/v), purified water, sodium iodide

ADVERSE REACTION

Distributed by: Perrigo Direct, Inc.

Peachtree City, GA 30269

www.PerrigoDriect.com 1-888-593-0593

Principal Display Panel

NDC 50804-088-10

GoodSense®

Iodine

Tincture U.S.P.

First Aid Antiseptic

For external use only

CAUTION: POISON

1 FL OZ (30 mL)